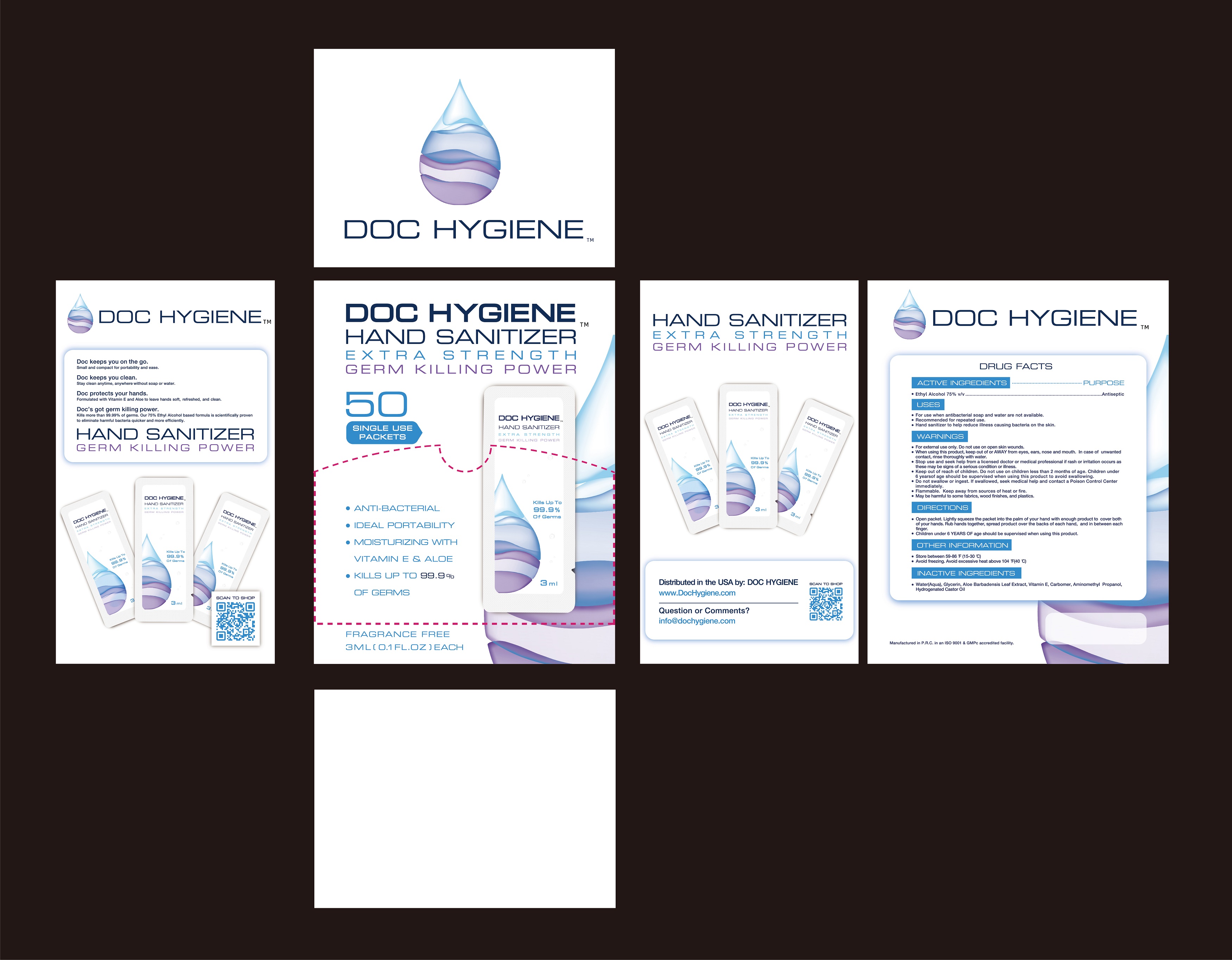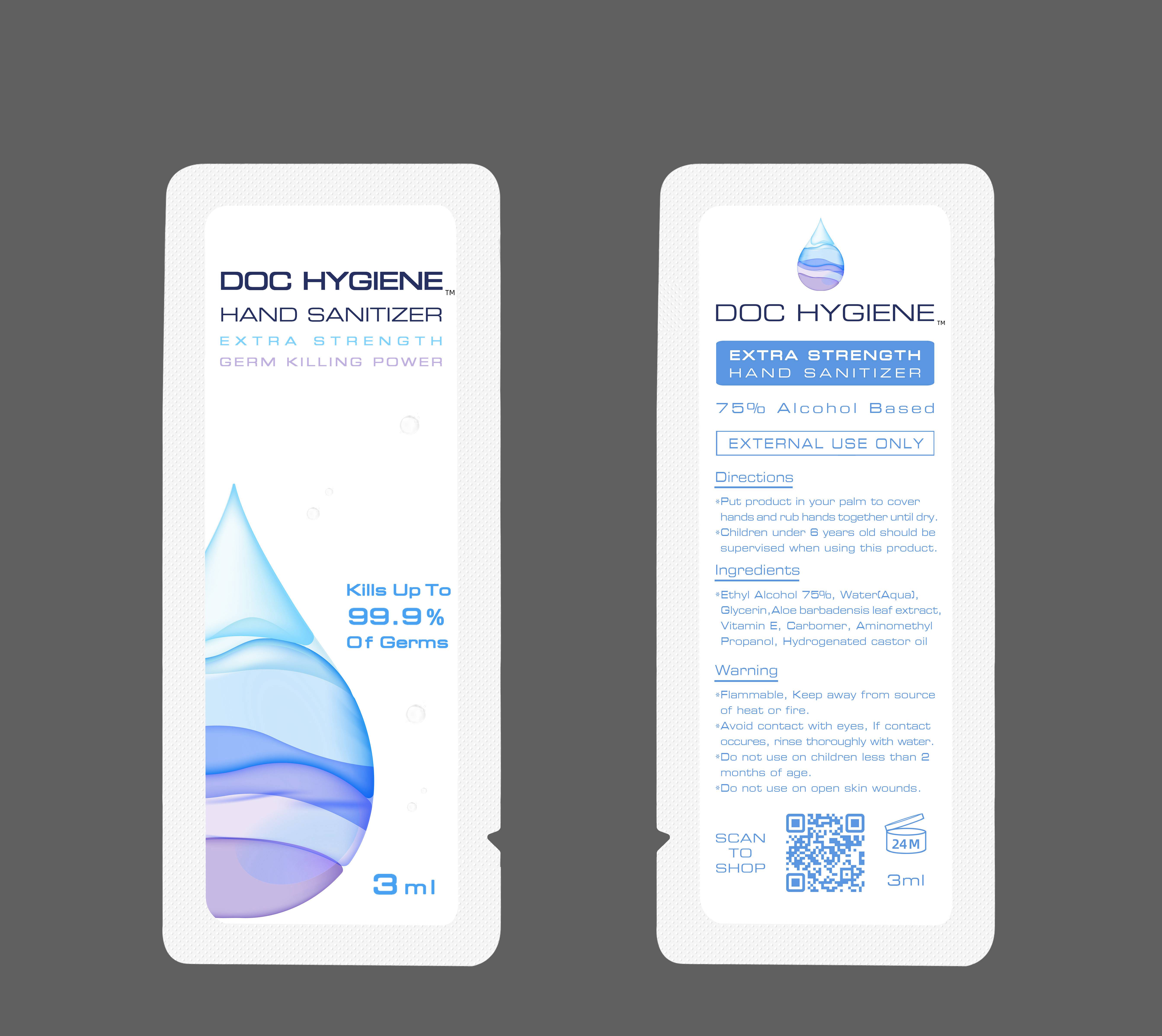 DRUG LABEL: Hand Sanitizer
NDC: 78765-001 | Form: GEL
Manufacturer: Great health companion Medical device technology group co., LTD
Category: otc | Type: HUMAN OTC DRUG LABEL
Date: 20200606

ACTIVE INGREDIENTS: ALCOHOL 75 mL/100 mL
INACTIVE INGREDIENTS: ALPHA-TOCOPHEROL ACETATE; AMINOMETHYLPROPANOL; ALOE VERA LEAF; PEG-40 CASTOR OIL; WATER; CARBOMER 1342; GLYCERIN

hand sanitizer 75% alcohol based

ACTIVE INGREDIENT(S)

Ethyl alcohol 75% v/v.

Purpose

Antiseptic

Use

For use when antibacterial soap and water are not available.
Recommended for repeated use.
Hand sanitizer to help reduce illness causing bacteria on the skin.

Warnings

For external use only. Do not use on open skin wounds.
When using this product, keep out or AWAY from eyes, ears, nose and mouth. In case of unwanted, rinse thoroughly with water.
Stop use and seek help form a licensed doctor or medical professional if rash or irritation occurs as these may be signs of a serious condition or illness.
Keep out of reach of children. Do not use on children less than 2 months of age. Children under 6 years of age should be supervised when using this product to avoid swallowing.
Do not swallow or ingest. If swallowed, seek medical help and contact a Poison Control Center immediately.
Flammable. Keep away from sources of heat or fire.

May be harmful to some fabrics, wood finishes and plastics.

Do not use

on children less than 2 months of age.

on open skin wounds.e

WHEN USING

keep out of eyes,ears and mouth.In case of contact with eyes, rinse thoroughly with water.

STOP USE

Stop use and ask a doctor if irritation or rash occurs.

These maybe signs of a serious condition.

KEEP OUT OF REACH OF CHILDREN

If swallowed, get medical help per contact a Poison Control Center right away.

Directions

Open packet. Lightly squeeze the packet into the palm of your hand with enough product to cover both of hands. Rub hands together, spread product over the backs of each hand, and in between each finger.
Children under 6 years of age should be supervised when using this product.

Other Information

Store between 59-86 ℉ (15-30℃).

Avoid freezing. Avoid excessive heat above 104 ℉ (40 ℃).

Inactive ingredients

Water(Aqua), Glycerin, Aloe barbadensis leaf extract, Carbomer, Aminomethyl Propanol, Hydrogenated castor oil, Tocopheryl acetate